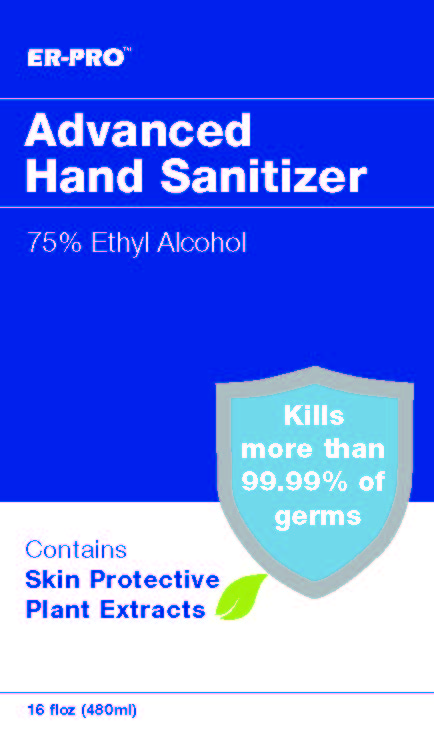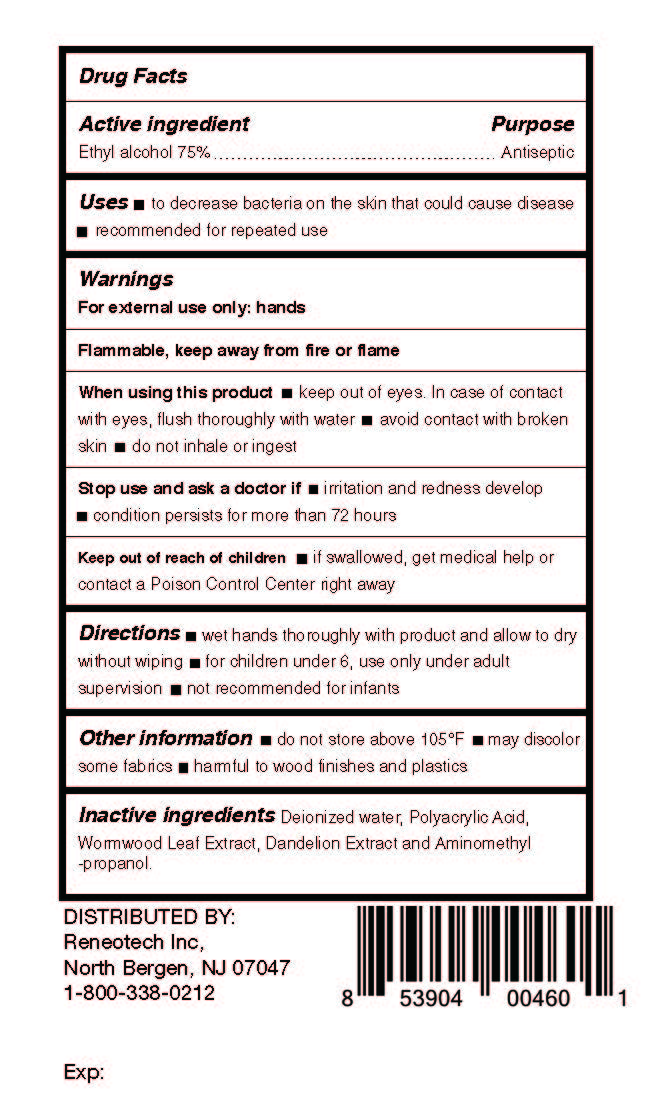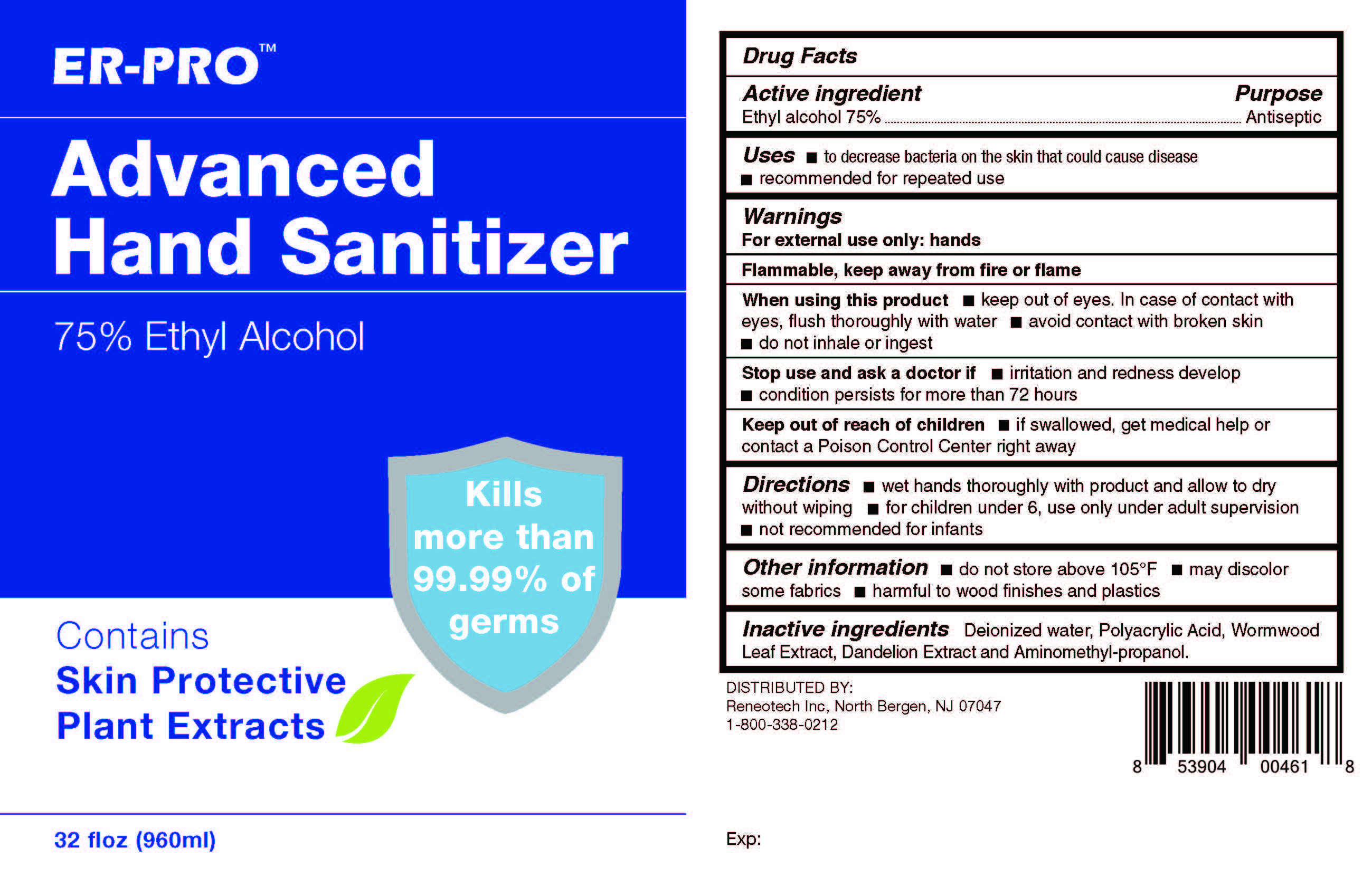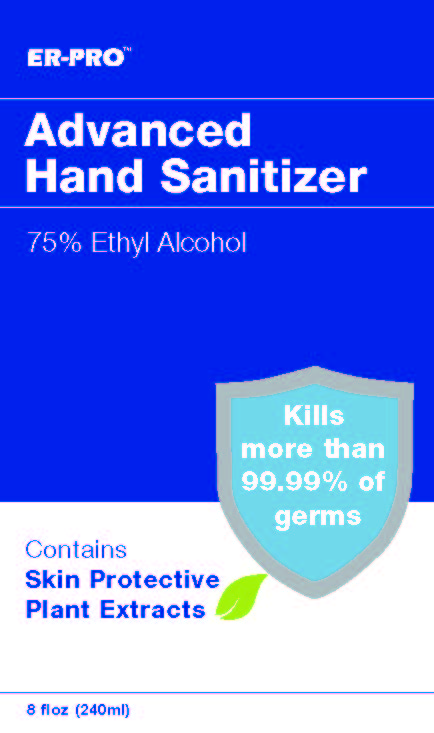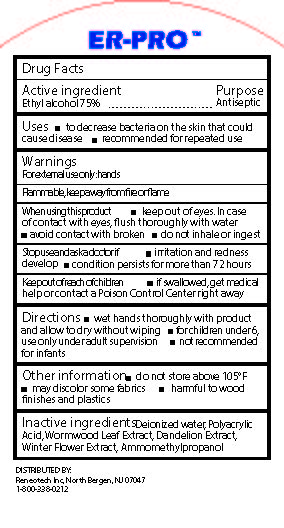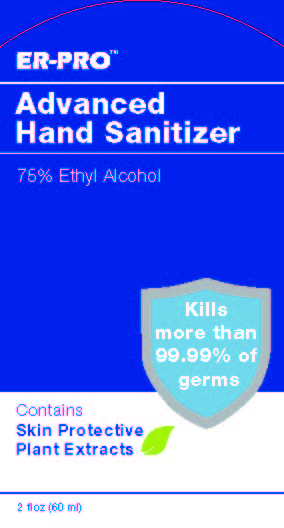 DRUG LABEL: Hand Sanitizer
NDC: 79991-001 | Form: GEL
Manufacturer: Reneotech Inc
Category: otc | Type: HUMAN OTC DRUG LABEL
Date: 20200820

ACTIVE INGREDIENTS: ALCOHOL 75 mL/75 mL
INACTIVE INGREDIENTS: POLYACRYLIC ACID (250000 MW); WORMWOOD; WATER; AMINOMETHYLPROPANOL; TARAXACUM OFFICINALE ROOT

Handsanitizer

This is a hand sanitizer manufactured according to the Temporary Policy for Preparation of Certain Alcohol-Based Hand Sanitizer Products During the Public Health Emergency (CoViD-19); Guidance for Industry.

The hand sanitizer is manufactured using only the following United States Pharmacopoeia (USP) grade ingredients in the preparation of the product (percentage in final product formulation) consistent with World Health Organization (WHO) recommendations:

1. Isopropyl Alcohol (75%, v/v) in an aqueous solution denatured according to Alcohol and Tobacco Tax and Trade Bureau regulations in 27 CFR part 20.
2. Glycerol (1.45% v/v).
3. Hydrogen peroxide (0.125% v/v).
4. Sterile distilled water or boiled cold water.

The firm does not add other active or inactive ingredients. Different or additional ingredients may impact the quality and potency of the product.

Active Ingredient(s)

Ethlyl Alcohol 75% v/v. Purpose: Antiseptic

Purpose

Antiseptic, Hand Sanitizer

Use

Uses

- To decrease bacteria on the skin that could cause disease
- Recommended for repeat use

Warnings

For external use only. Flammable. Keep away from fire or flame

Do not use

- in children less than 2 months of age
- on open skin wounds

When using this product

- Keep out of eyes, incased of contact with eyes, flush thoroughly with water
- Avoid contact with broken skin
- Do not inhale or ingest

Stop use and ask a doctor if

- Irritation and redness develop
- Condition persists for more than 72 hours

Keep out of reach of children

- . If swallowed, get medical help or contact a Poison Control Center right away.

Directions

- Wet hands thoroughly with product and allow to dry without wiping
- For Children under 6, use only under adult supervision
- Not recommended for infants

Other information

- Do not store above 105°F
- May discolor some fabrics
- Harmful to woodfinishes and plastics

Inactive ingredients

Deionized Water, Polyacrylic Acid, Wormwood Leaf Extract, Dandelion Extract, Aminomethyl Propanol.

RECENT MAJOR CHANGES

- usage
- warnings

Package Label - Principal Display Panel

- 59.1471 ml NDC: 79991-001-05
- 236.588 ml NDC: 79991-001-08

- 480 ml NDC: 79991-001-10
- 946.353 ml NDC: 79991-001-12